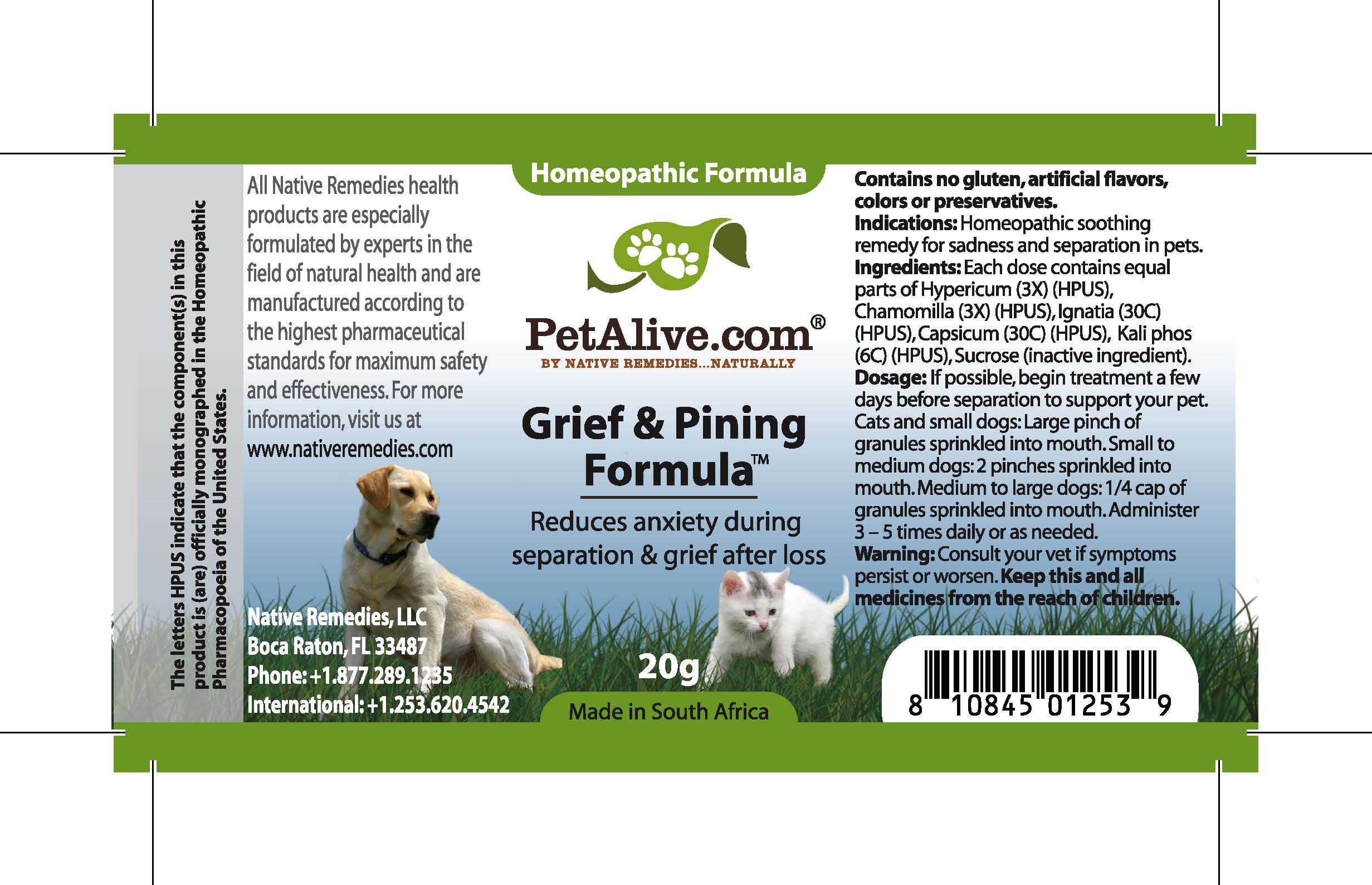 DRUG LABEL: Grief and Pining Formula
NDC: 68647-150 | Form: GRANULE
Manufacturer: Feelgood Health
Category: homeopathic | Type: OTC ANIMAL DRUG LABEL
Date: 20100903

ACTIVE INGREDIENTS: HYPERICUM PERFORATUM 3 [hp_X]/40 mg; CHAMOMILE 3 [hp_X]/40 mg; STRYCHNOS IGNATII SEED 30 [hp_C]/40 mg; AJI PEPPER 30 [hp_C]/40 mg; POTASSIUM PHOSPHATE 6 [hp_C]/40 mg
INACTIVE INGREDIENTS: SUCROSE 20000 mg/20000 mg

GRIEF AND PINING FORMULA

PURPOSE

Reduces anxiety during separation and grief after loss

INDICATIONS AND USAGE

Indications: Homeopathic soothing remedy for sadness and separation in pets.

DOSAGE AND ADMINISTRATION

Dosage: If possible, begin treatment a few days before separation to support your pet. Cats and dogs under 20 lbs: Large pinch of granules sprinkled into mouth. Dogs 20-50 lbs: 2 pinches sprinkled into mouth. Dogs over 50 lbs: 1/4 cap of granules sprinkled into mouth. Administer 3-5 times daily or as needed.

GENERAL PRECAUTIONS

Caution: Consult your vet if symptoms persist or worsen. Keep this and all medicines from the reach of children.

ACTIVE INGREDIENT

Ingredients: Each dose contains equal parts of Hypericum (3X) (HPUS),Chamomilla (3X) (HPUS), Ignatia (30C) (HPUS), Capsicum (30C) (HPUS), Kali phos (6C) (HPUS)

Sucrose (inactive ingredient).

WARNINGS

Contains no gluten, artificial flavors, colors or preservatives.

PATIENT COUNSELING INFORMATION

All Native Remedies health products are especially formulated by experts in the field of natural health and are manufactured according to the highest pharmaceutical standards for maximum safety and effectiveness. For more information, visit us at www.nativeremedies.com

Distributed by

Native Remedies, LLC

6531 Park of Commerce Blvd.

Suite 160

Boca Raton, FL 33487

Phone: 1.877.289.1235

International: + 1.561.999.8857

The letters HPUS indicate that the component(s) in this product is (are) officially monographed in the Homeopathic Pharmacopoeia of the United States.

KEEP OUT OF REACH OF CHILDREN

Keep this and all medicines out of reach of children.